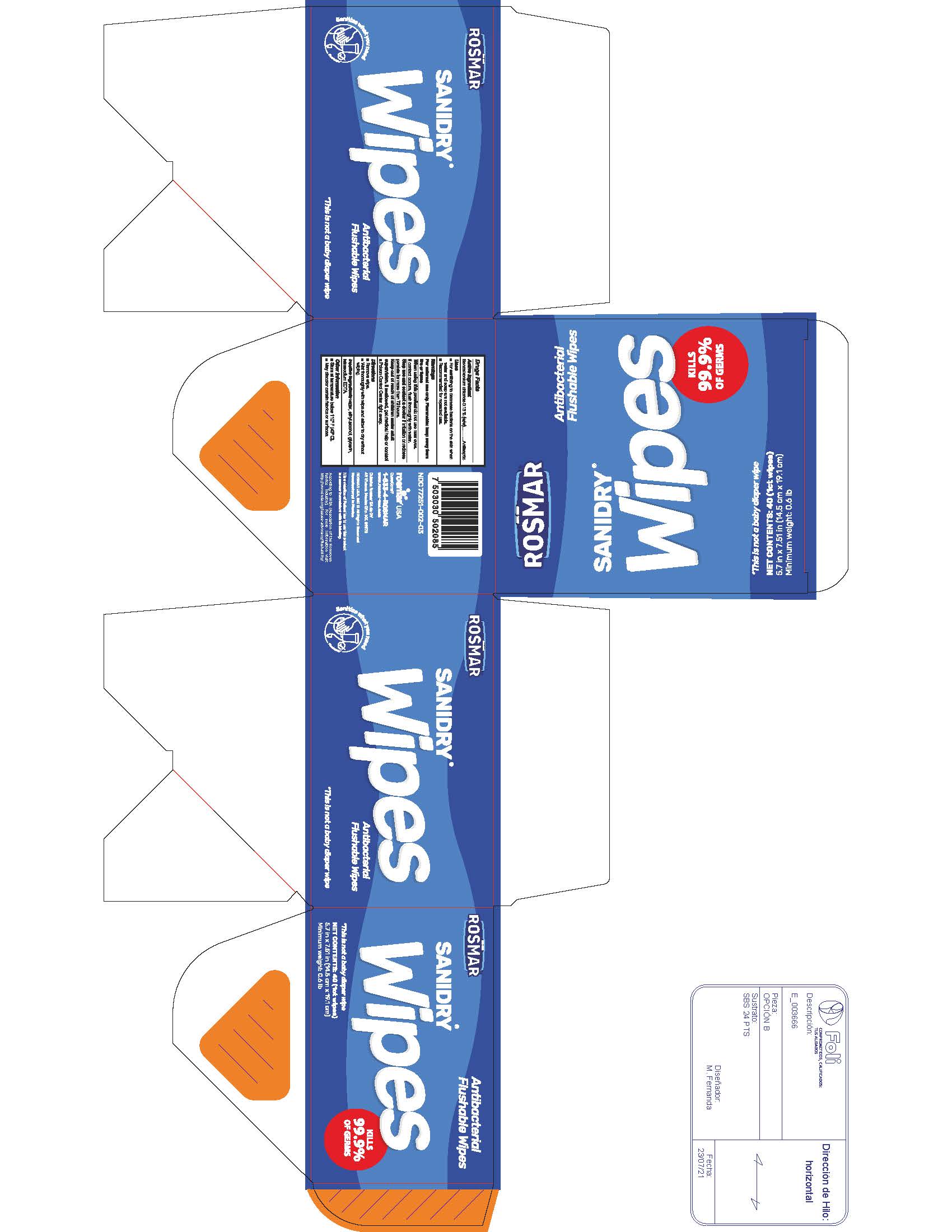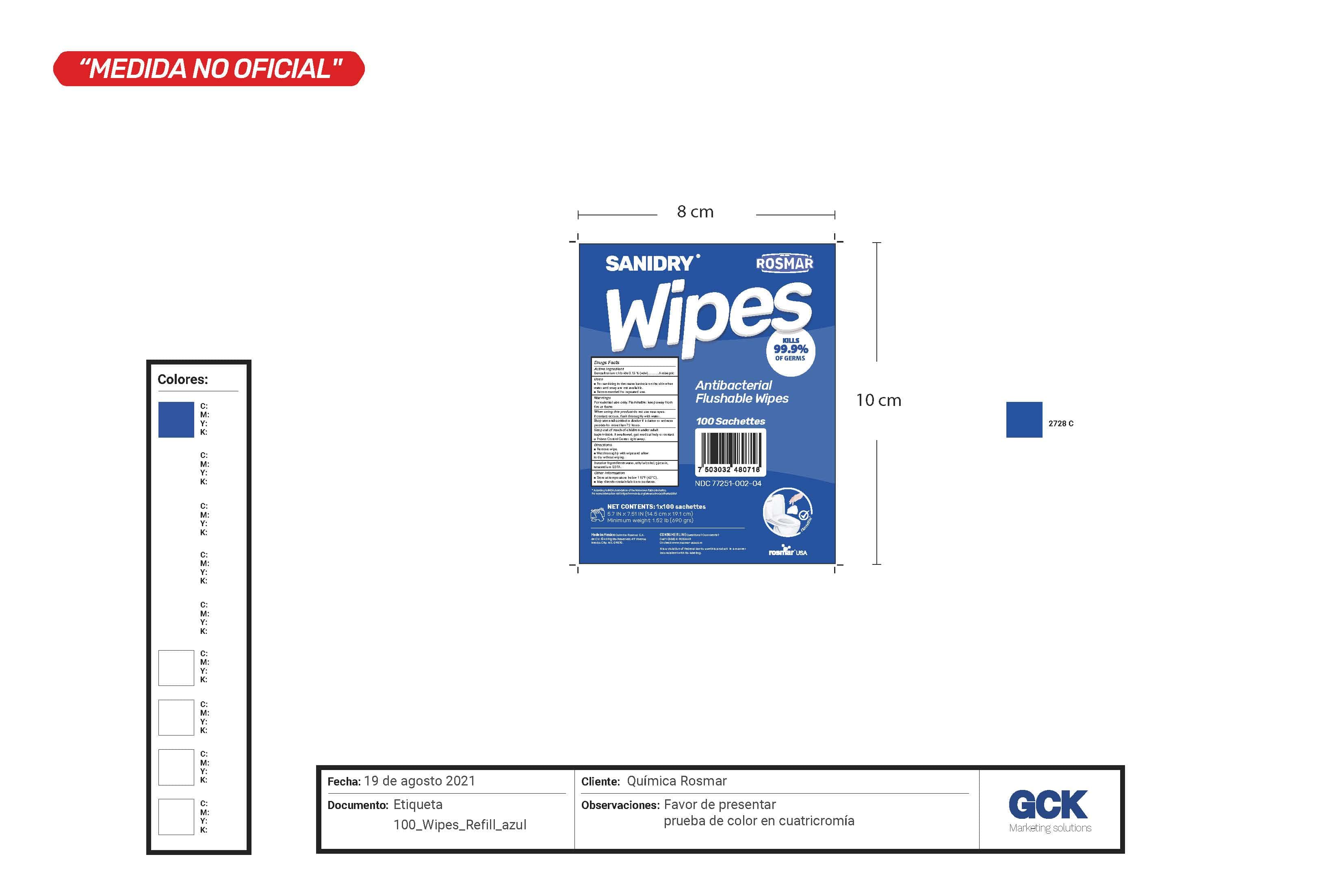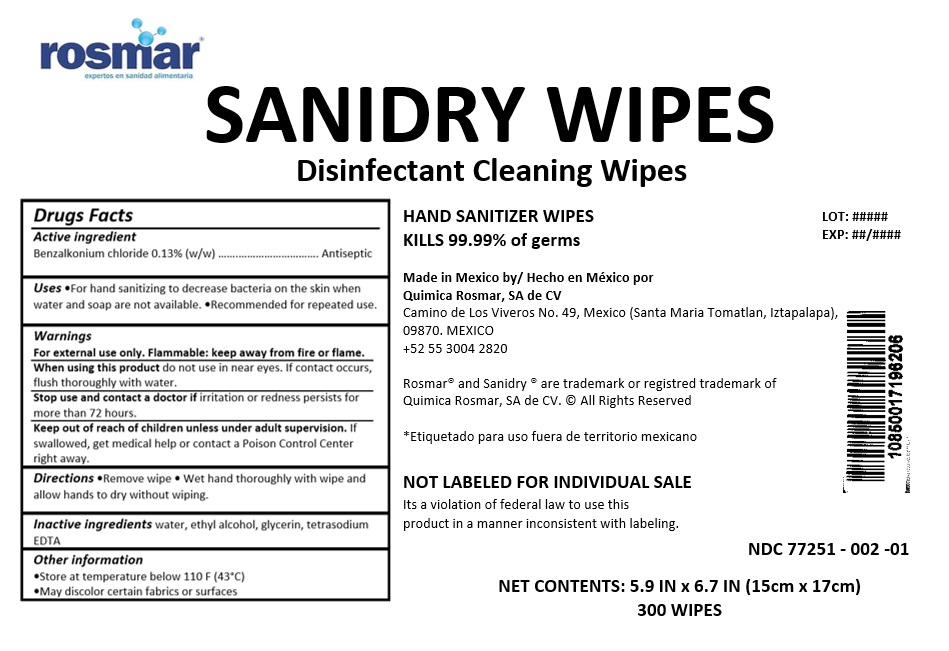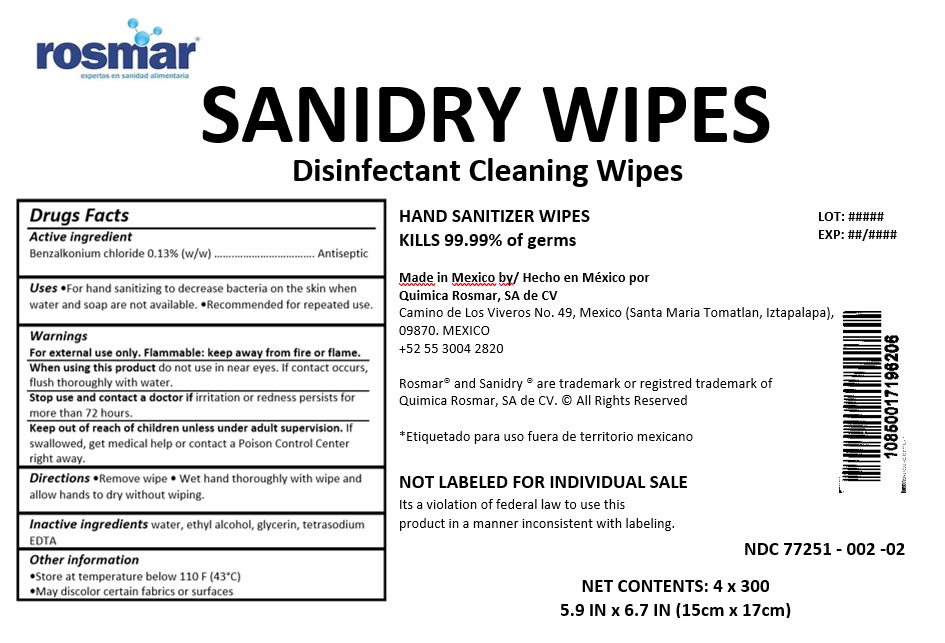 DRUG LABEL: Sanidry Wipes
NDC: 77251-002 | Form: CLOTH
Manufacturer: QUIMICA ROSMAR S.A. DE C.V.
Category: otc | Type: HUMAN OTC DRUG LABEL
Date: 20210909

ACTIVE INGREDIENTS: BENZALKONIUM CHLORIDE 0.133 1/100 1
INACTIVE INGREDIENTS: WATER; ALCOHOL; GLYCERIN; EDETATE SODIUM

77251-002 Sanidry Flushable Wipes

Active ingredient

Benzalkonium chloride 0.13% (w/w)

Purpose

Antiseptic

Uses

- For hand sanitizing to decrease bacteria on the skin when water and soap are not available
- Recommended for repeated use.

Warnings

For external use only. Flammable: keep away from fire or flame.

When using this product do not use in near eyes. If contact occurs, flush thoroughly with water.

Stop use and contact a doctor if irritation or redness persists for more than 72 hours.

Keep out of reach of children unless under adult supervision. If swallowed, get medical help or contact a Poison Control Center right away.

Directions

- Remove wipe
- Wet hand thoroughly with wipe and allow hands to dry without wiping.

Inactive ingredients

water, ethyl alcohol, glycerin, tetrasodium EDTA

Other information

- Store at temperature below 110 F (43°C)
- May discolor certain fabrics or surfaces

PACKAGE LABEL

300 Wipes - NDC 77251-002-01

1200 Wipes - NDC 77251-002-02

40 wipes - NDC 77251-002-03

100 wipes - NDC 77251-002-04